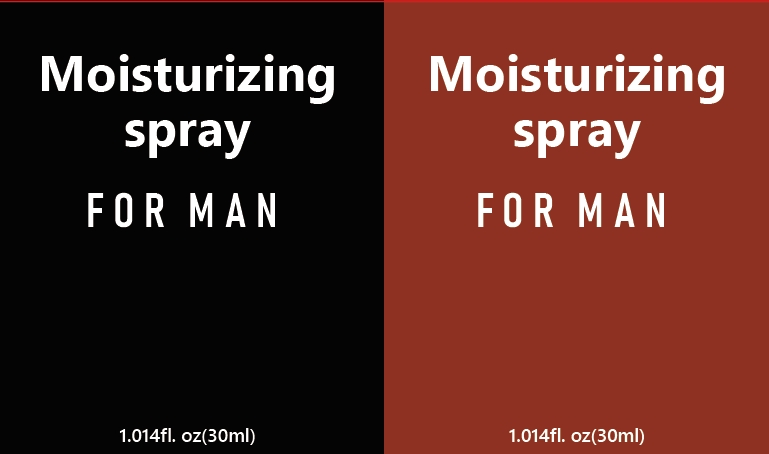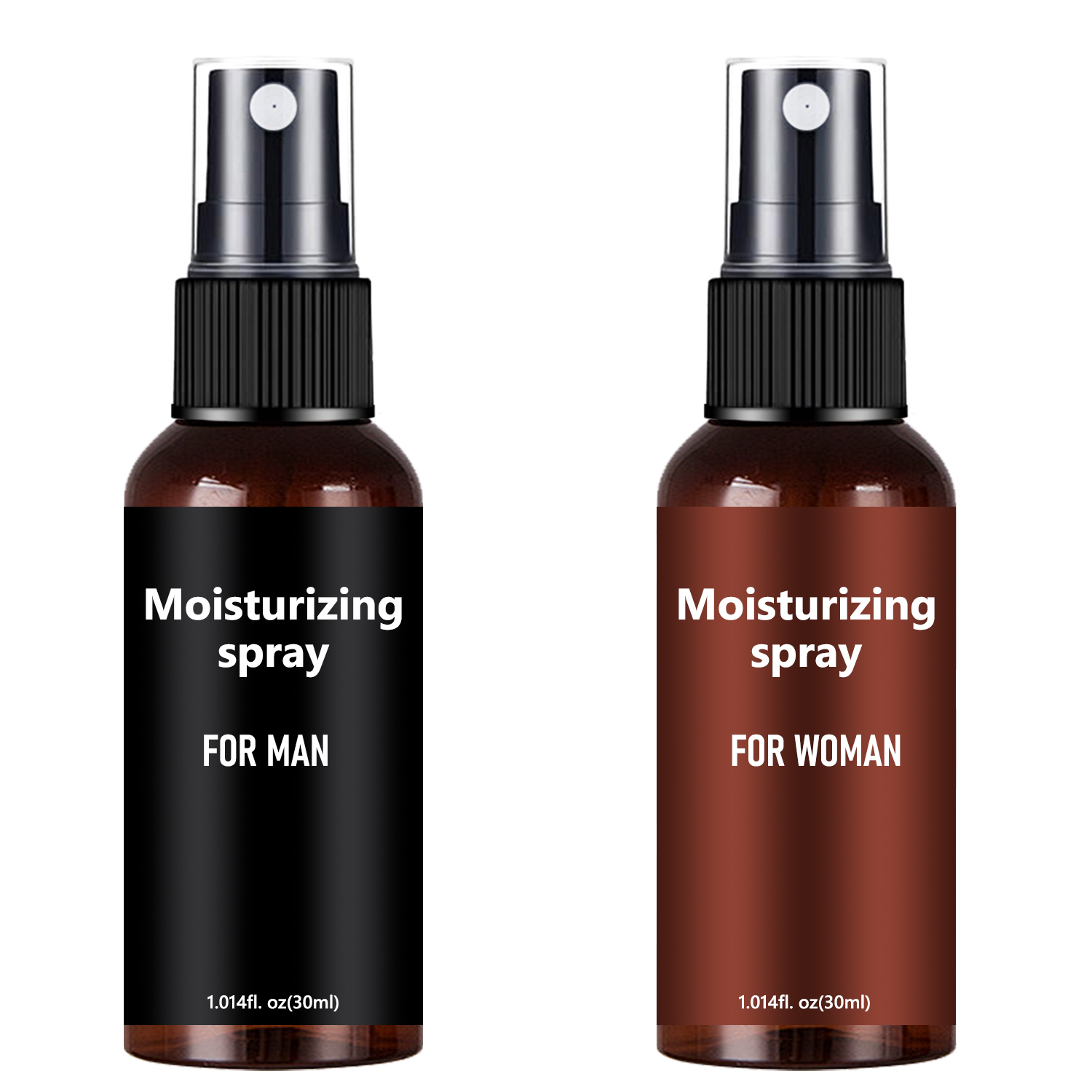 DRUG LABEL: MoisturizingSpray
NDC: 84025-227 | Form: CREAM
Manufacturer: Guangzhou Yanxi Biotechnology Co., Ltd
Category: otc | Type: HUMAN OTC DRUG LABEL
Date: 20241021

ACTIVE INGREDIENTS: GLYCERIN 3 mg/100 mL; ALOE BARBADENSIS LEAF EXTRACT 5 mg/100 mL
INACTIVE INGREDIENTS: WATER

DOSAGE AND ADMINISTRATION

use as man and women's body

WARNINGS

keep out of children

INACTIVE INGREDIENT

Aqua

INDICATIONS AND USAGE

For man and women's body care.

keep out of children

PURPOSE

Helps by prolonging the time it takes to ejaculate.